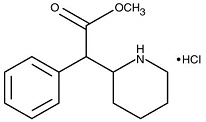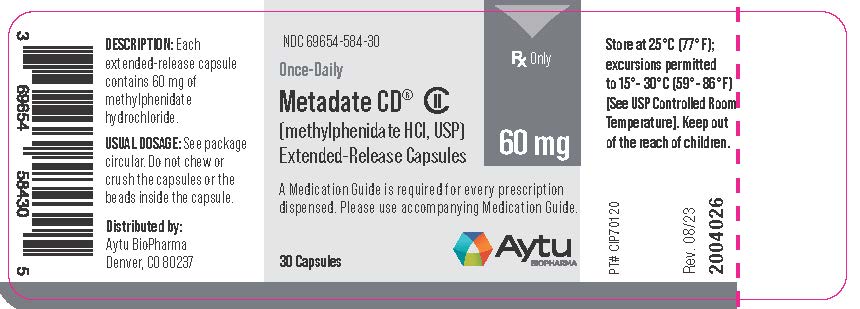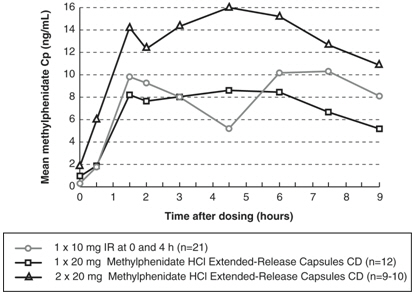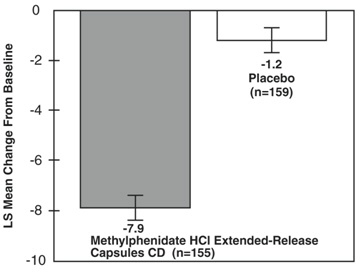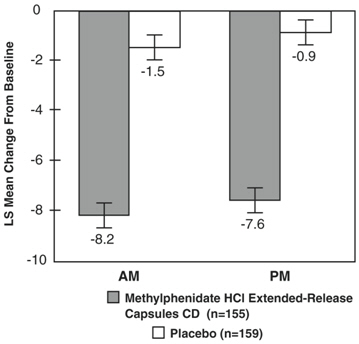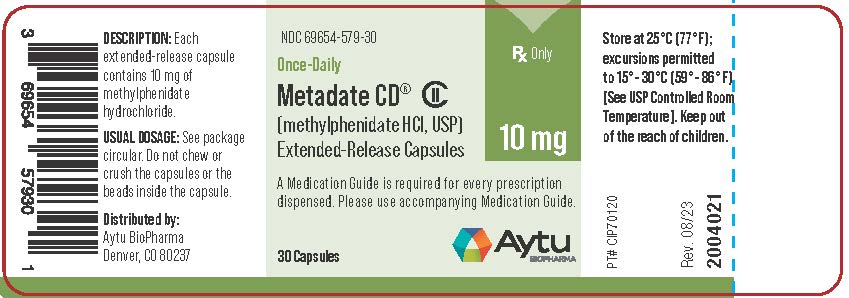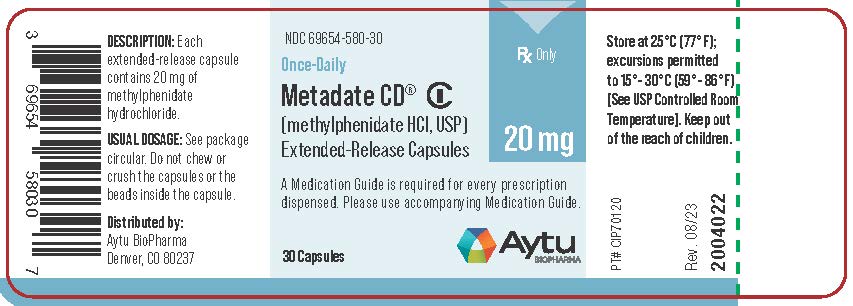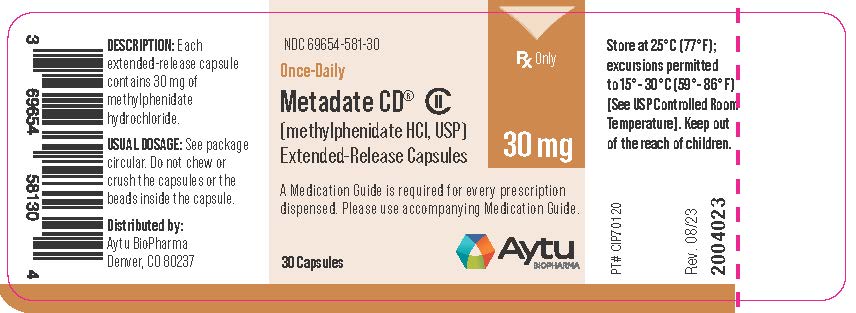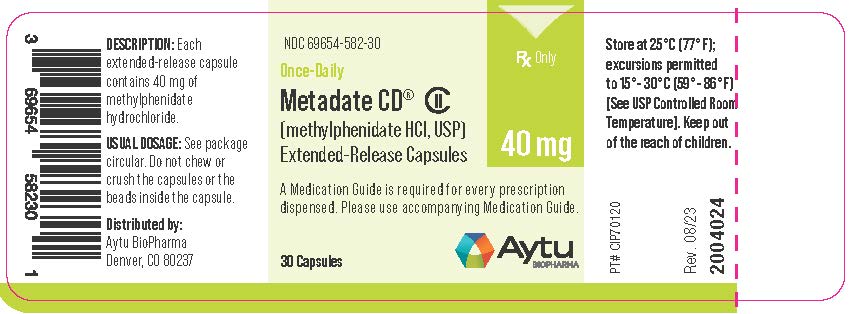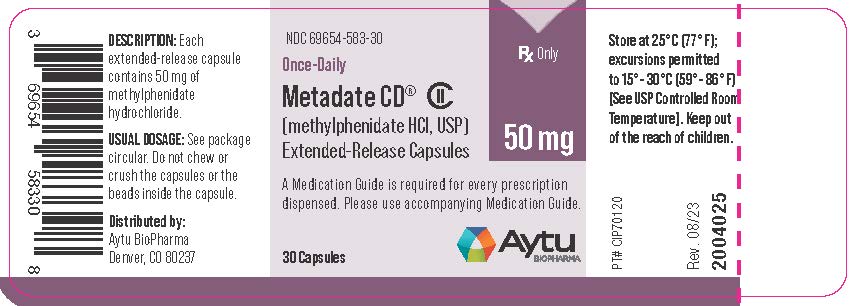 DRUG LABEL: METADATE CD
NDC: 69654-579 | Form: CAPSULE, EXTENDED RELEASE
Manufacturer: Aytu BioPharma, Inc.
Category: prescription | Type: HUMAN PRESCRIPTION DRUG LABEL
Date: 20251118
DEA Schedule: CII

ACTIVE INGREDIENTS: METHYLPHENIDATE HYDROCHLORIDE 10 mg/1 1
INACTIVE INGREDIENTS: POVIDONE, UNSPECIFIED; HYPROMELLOSE, UNSPECIFIED; POLYETHYLENE GLYCOL, UNSPECIFIED; DIBUTYL SEBACATE; FD&C BLUE NO. 2; FERRIC OXIDE YELLOW

HIGHLIGHTS OF PRESCRIBING INFORMATION

These highlights do not include all the information needed to use METADATE CD®safely and effectively. See full prescribing information for METADATE CD.
METADATE CD (methylphenidate hydrochloride) extended-release capsules, CII
Initial U.S. Approval: 1955

WARNING: ABUSE, MISUSE, AND ADDICTION

See full prescribing information for complete boxed warning.

METADATE CD has a high potential for abuse and misuse, which can lead to the development of a substance use disorder, including addiction. Misuse and abuse of CNS stimulants, including METADATE CD, can result in overdose and death (5.1, 9.2, 10):

- Before prescribing METADATE CD, assess each patient’s risk for abuse, misuse, and addiction.
- Educate patients and their families about these risks, proper storage of the drug, and proper disposal of any unused drug.
- Throughout treatment, reassess each patient’s risk and frequently monitor for signs and symptoms of abuse, misuse, and addiction.

RECENT MAJOR CHANGES

Indications and Usage (1) 09/2025

Warnings and Precautions (5.7) 09/2025

1 INDICATIONS AND USAGE

METADATE CD is a central nervous system (CNS) stimulant indicated for the treatment of Attention Deficit Hyperactivity Disorder (ADHD) in pediatric patients 6 to 15 years of age (1)

Limitations of Use

The use of METADATE CD is not recommended in pediatric patients younger than 6 years of age because they had higher exposure and a higher incidence of adverse reactions (e.g., weight loss) than patients 6 years and older at the same dosage. (5.7, 8.4)

2 DOSAGE AND ADMINISTRATION

- Take orally once daily in the morning, before breakfast.
- Swallow whole with the aid of liquids, or sprinkle contents onto a small amount of applesauce and give immediately.
- Do not crush or chew the capsule or capsule contents (2.1)
- Recommended starting dose is 20 mg once daily. Dosage may be increased 10-20 mg at weekly intervals; do not exceed 60 mg per day (2.2)

3 DOSAGE FORMS AND STRENGTHS

Extended-release capsules: 10 mg, 20 mg, 30 mg, 40 mg, 50 mg, 60 mg (3)

4 CONTRAINDICATIONS

- Known hypersensitivity to methylphenidate or other components of METADATE CD (4)
- Concurrent treatment with a monoamine oxidase inhibitor (MAOI), or use of an MAOI within the preceding 14 days (4)
- Use in patients with patients with hereditary problems of fructose intolerance, glucose-galactose malabsorption, or sucrase-isomaltase insufficiency (4)

5 WARNINGS AND PRECAUTIONS

- Risks to Patients with Serious Cardiac Disease: Avoid use in patients with known structural cardiac abnormalities, cardiomyopathy, serious cardiac arrhythmias, coronary artery disease, or other serious cardiac disease. (5.2)
- Increased Blood Pressure and Heart Rate: Monitor blood pressure and pulse. (5.3)
- Psychiatric Adverse Reactions: Prior to initiating METADATE CD, screen patients for risk factors for developing a manic episode. If new psychotic or manic symptoms occur, consider discontinuing METADATE CD. (5.4)
- Priapism: If abnormally sustained or frequent and painful erections occur, patients should seek immediate medical attention. (5.5)
- Peripheral Vasculopathy, including Raynaud’s Phenomenon: Careful observation for digital changes is necessary during METADATE CD treatment. Further clinical evaluation (e.g., rheumatology referral) may be appropriate for patients who develop signs or symptoms of peripheral vasculopathy. (5.6)
- Long-Term Suppression of Growth in Pediatric Patients: Closely monitor growth (height and weight) in pediatric patients. Pediatric patients not growing or gaining height or weight as expected may need to have their treatment interrupted. (5.7)
- Acute Angle Closure Glaucoma: METADATE CD-treated patients considered at risk for acute angle closure glaucoma (e.g., patients with significant hyperopia) should be evaluated by an ophthalmologist. (5.8)
- Increased Intraocular Pressure (IOP) and Glaucoma: Prescribe METADATE CD to patients with open-angle glaucoma or abnormally increased IOP only if the benefit of treatment is considered to outweigh the risk. Closely monitor patients with a history of increased IOP or open angle glaucoma. (5.9)
- Motor and Verbal Tics, and Worsening of Tourette’s Syndrome: Before initiating METADATE CD, assess the family history and clinically evaluate patients for tics or Tourette’s syndrome. Regularly monitor patients for the emergence or worsening of tics or Tourette’s syndrome. Discontinue treatment if clinically appropriate. (5.10)

6 ADVERSE REACTIONS

The most common adverse reactions (≥ 5% and twice the rate of placebo) were anorexia and insomnia (6.1)

To report SUSPECTED ADVERSE REACTIONS, contact Aytu BioPharma at 1-855-298-8246 or FDA at 1-800-FDA-1088 orwww.fda.gov/medwatch

7 DRUG INTERACTIONS

Antihypertensive Drugs: Monitor blood pressure. Adjust dosage of antihypertensive drug as needed (7)

FULL PRESCRIBING INFORMATION

WARNING: ABUSE, MISUSE, AND ADDICTION

METADATE CD has a high potential for abuse and misuse, which can lead to the development of a substance use disorder, including addiction. Misuse and abuse of CNS stimulants, including METADATE CD, can result in overdose and death [see Overdosage (10)] , and this risk is increased with higher doses or unapproved methods of administration, such as snorting or injection.

Before prescribing METADATE CD, assess each patient’s risk for abuse, misuse, and addiction. Educate patients and their families about these risks, proper storage of the drug, and proper disposal of any unused drug. Throughout METADATE CD treatment, reassess e ach patient’s risk of abuse, misuse, and addiction and frequently monitor for signs and symptoms of abuse, misuse, and addiction [see Warnings and Precautions (5.1) and Drug Abuse and dependence (9.2)] .

1 INDICATIONS AND USAGE

METADATE CD is indicated for the treatment of Attention Deficit Hyperactivity Disorder (ADHD) in pediatric patients 6 to 15 years of age.

Limitations of Use

The use of METADATE CD is not recommended in pediatric patients younger than 6 years of age because they had higher plasma exposure and a higher incidence of adverse reactions (e.g. weight loss) than patients 6 years and older at the same dosage [see Warnings and Precautions (5.7). Use in Specific Populations (8.4)] .

2 DOSAGE AND ADMINISTRATION

2.1 Pretreatment Screening

Prior to treating patients with METADATE CD, assess:

- for the presence of cardiac disease (i.e., perform a careful history, family history of sudden death or ventricular arrhythmia, and physical exam) [see Warnings and Precautions (5.10)] .
- the family history and clinically evaluate patients for motor or verbal tics or Tourette’s syndrome before initiating METADATE CD [see Warnings and Precautions (5.10)] .

2.2 Dosage Recommendations

The recommended starting dose of METADATE CD is 20 mg once daily. Dosage may be adjusted in weekly 10 mg to 20 mg increments to the maximum recommended dose of 60 mg per day.

Dosage should be individualized according to the needs and responses of the patient.

2.3 Administration Instructions

Administer METADATE CD orally once daily in the morning, before breakfast.

Swallow the capsule whole with the aid of liquids. Alternatively, open the capsule and sprinkle the contents onto a small amount (tablespoon) of applesauce and administer immediately. Do not store for future use. Drink fluids following the intake of the sprinkled capsule contents with applesauce. The capsules and the capsule contents must not be crushed or chewed.

2.4 Dosage Reduction and Discontinuation

If paradoxical aggravation of symptoms or other adverse reactions occur, reduce dosage or, if necessary, discontinue METADATE CD. If improvement is not observed after appropriate dosage adjustment over a one-month period, discontinue METADATE CD.

3 DOSAGE FORMS AND STRENGTHS

METADATE CD extended-release capsules are available in the following dosage strengths (see Table 1):

Table 1: Strengths and Identifying Characteristics of METADATE CD
Strength | Capsule Color (cap/body) | Imprinting on Capsule Cap | Imprinting on Capsule Body
10 mg | green/white | “AYTU 579” in white letters | “10 mg” in black letters
20 mg | blue/white | “AYTU 580” in white letters | “20 mg” in black letters
30 mg | reddish-brown/white | “AYTU 581” in white letters | “30 mg” in black letters
40 mg | yellow ivory/white | “AYTU 582” in black letters | “40 mg” in black letters
50 mg | purple/white | “AYTU 583” in white letters | “50 mg” in black letters
60 mg | white/white capsules | “AYTU 584” in black letters | “60 mg” in black letters

4 CONTRAINDICATIONS

METADATE CD is contraindicated in patients with:

- known hypersensitivity to methylphenidate or other component of METADATE CD. Angioedema has been reported in patients treated with METADATE CD. Anaphylactic reactions have been reported in patients treated with other methylphenidate products [see Adverse Reactions (6)] .
- Concomitant treatment with monoamine oxidase inhibitors (MAOIs), or within 14 days following discontinuation of treatment with an MAOI, because of the risk of hypertensive crisis [see Drug Interactions (7)] .
- METADATE CD contains sucrose. Therefore, patients with hereditary problems of fructose intolerance, glucose-galactose malabsorption, or sucrase-isomaltase insufficiency should not take this medicine.

5 WARNINGS AND PRECAUTIONS

5.1 Abuse, Misuse, and Addiction

METADATE CD has a high potential for abuse and misuse. The use of METADATE CD exposes individuals to the risks of abuse and misuse, which can lead to the development of a substance use disorder, including addiction. METADATE CD can be diverted for non-medical use into illicit channels or distribution [see Drug Abuse and Dependence (9.2)] . Misuse and abuse of CNS stimulants, including METADATE CD, can result in overdose and death [see Overdosage (10)] , and this risk is increased with higher doses or unapproved methods of administration, such as snorting or injection.

Before prescribing METADATE CD, assess each patient’s risk for abuse, misuse, and addiction. Educate patients and their families about these risks and proper disposal of any unused drug. Advise patients to store METADATE CD in a safe place, preferably locked, and instruct patients to not give METADATE CD to anyone else. Throughout METADATE CD treatment, reassess each patient’s risk of abuse, misuse, and addiction and frequently monitor for signs and symptoms of abuse, misuse, and addiction.

5.2 Risks to Patients with Serious Cardiac Disease

Sudden death has been reported in patients with structural cardiac abnormalities or other serious cardiac disease who were treated with CNS stimulants at the recommended dosage.

Avoid METADATE CD use in patients with known structural cardiac abnormalities, cardiomyopathy, serious cardiac arrhythmia, coronary artery disease, or other serious cardiac problems.

5.3 Increased Blood Pressure and Heart Rate

CNS stimulants cause an increase in blood pressure (mean increase approximately 2 to 4 mmHg) and heart rate (mean increase approximately 3 to 6 bpm). Some patients may have larger increases.

Monitor all METADATE CD treated patients for hypertension and tachycardia.

5.4 Psychiatric Adverse Reactions

Exacerbation of Pre-Existing Psychosis

CNS stimulants may exacerbate symptoms of behavior disturbance and thought disorder in patients with a pre-existing psychotic disorder.

Induction of a Manic Episode in Patients with Bipolar Disorder

CNS stimulants may induce a manic or mixed episode in patients. Prior to initiating METADATE CD treatment, screen patients for risk factors for developing a manic episode (e.g., comorbid or history of depressive symptoms or a family history of suicide, bipolar disorder, or depression).

New Psychotic or Manic Symptoms

CNS stimulants, at the recommended dosages, may cause psychotic or manic symptoms (e.g., hallucinations, delusional thinking, or mania) in patients without a prior history of psychotic illness or mania. In a pooled analysis of multiple short-term, placebo- controlled studies of CNS stimulants, psychotic or manic symptoms occurred in approximately 0.1% of CNC stimulant-treated patients, compared to 0% of placebo-treated patients If such symptoms occur, consider discontinuing METADATE CD.

5.5 Priapism

Prolonged and painful erections, sometimes requiring surgical intervention, have been reported with methylphenidate use in both adult and pediatric male patients. Although priapism was not reported with methylphenidate initiation, it developed after some time on methylphenidate, often subsequent to an increase in dosage. Priapism also occurred during methylphenidate withdrawal (drug holidays or during discontinuation).

METADATE CD-treated patients who develop abnormally sustained or frequent and painful erections should seek immediate medical attention.

5.6 Peripheral Vasculopathy, including Raynaud’s Phenomenon

CNS stimulants, including METADATE CD, used to treat ADHD are associated with peripheral vasculopathy, including Raynaud’s phenomenon. Signs and symptoms are usually intermittent and mild; however, sequelae have included digital ulceration and/or soft tissue breakdown. Effects of peripheral vasculopathy, including Raynaud’s phenomenon, were observed in post-marketing reports and at the therapeutic dosages of CNS stimulants in all age groups throughout the course of treatment. Signs and symptoms generally improved after dosage reduction in or discontinuation of the CNS stimulant.

Careful observation for digital changes is necessary during METADATE CD treatment. Further clinical evaluation (e.g., rheumatology referral) may be appropriate for METADATE CD-treated patients who develop signs of symptoms of peripheral vasculopathy.

5.7 Long-Term Suppression of Growth in Pediatric Patients

METADATE CD is not approved for use and is not recommended in pediatric patients below 6 years of age [see Use in Specific Population (8.4)] .

CNS stimulants have been associated with weight loss and slowing of growth rate in pediatric patients.

Careful follow-up of weight and height in children ages 7 to 10 years who were randomized to either methylphenidate or non- medication treatment groups over 14 months, as well as in naturalistic subgroups of newly methylphenidate-treated and non- medication treated children over 36 months (to the ages of 10 to 13 years), suggests that pediatric patients who received methylphenidate treatment for 7 days per week throughout the year had a temporary slowing in growth rate (on average, a total of about 2 cm less growth in height and 2.7 kg less growth in weight over 3 years), without evidence of growth rebound during this development period.

Closely monitor growth (weight and height) in METADATE CD-treated pediatric patients. Pediatric patients who are not growing or gaining height or weight as expected may need to have their treatment interrupted.

5.8 Acute Angle Closure Glaucoma

There have been reports of angle closure glaucoma associated with methylphenidate treatment. Although the mechanism is not clear, METADATE CD-treated patients considered at risk for acute angle closure glaucoma (e.g., patients with significant hyperopia) should be evaluated by an ophthalmologist.

5.9 Increased Intraocular Pressure and Glaucoma

There have been reports of an elevation of intraocular pressure (IOP) associated with methylphenidate treatment [see Adverse Reactions (6.2)].

Prescribe METADATE CD to patients with open-angle glaucoma or abnormally increased IOP only if the benefit of treatment is considered to outweigh the risk. Closely monitor METADATE CD-treated patients with a history of abnormally increased IOP or open angle glaucoma.

5.10 Motor and Verbal Tics, and Worsening of Tourette’s Syndrome

CNS stimulants, including methylphenidate, have been associated with the onset or exacerbation of motor and verbal tics. Worsening of Tourette’s syndrome has also been reported [see Adverse Reactions (6.2)] .

Before initiating METADATE CD, assess the family history and clinically evaluate patients for tics or Tourette’s syndrome. Regularly monitor METADATE CD-treated patients for the emergence or worsening of tics or Tourette’s syndrome, and discontinue treatment if clinically appropriate.

6 ADVERSE REACTIONS

The following are discussed in more detail in other sections of the labeling:

- Abuse, Misuse, and Addiction [see Warnings and Precautions (5.1), Drug Abuse and Dependence (9.2, 9.3)]
- Hypersensitivity to Methylphenidate and Other Component of METADATE CD [see Contraindications (4)]
- Hypertensive Crisis when Used Concomitantly with MAOIs [see Contraindications (4) and Drug Interactions (7)]
- Risks to Patients with Serious Cardiac Disease [see Warnings and Precautions (5.2)]
- Increased Blood Pressure and Heart Rate [see Warnings and Precautions (5.3)]
- Psychiatric Adverse Reactions [see Warnings and Precautions (5.4)]
- Priapism [see Warnings and Precautions (5.5)]
- Peripheral Vasculopathy, including Raynaud’s Phenomenon [see Warnings and Precautions (5.6)]
- Long-Term Suppression of Growth in Pediatric Patients [see Warnings and Precautions (5.7)]
- Acute Angle Closure Glaucoma [see Warnings and Precautions (5.8)]
- Increased Intraocular Pressure and Glaucoma [see Warnings and Precautions (5.9)]
- Motor and Verbal Tics, and Worsening of Tourette’s Syndrome [see Warnings and Precautions (5.10)]

6.1 Clinical Trials Experience

Because clinical trials are conducted under widely varying conditions, adverse reaction rates observed in the clinical trials of a drug cannot be directly compared to rates in the clinical trials of another drug and may not reflect the rates observed in practice.

Clinical trials experience with METADATE CD included 188 pediatric patients 6 to 15 years old with ADHD exposed to METADATE CD. Patients received METADATE CD 20 mg, 40 mg, and/or 60 mg per day. The 188 patients were evaluated in the following studies: Study 1, a 3-week placebo-controlled clinical study consisting of a total of 314 pediatric patients (ages 6 to 15 years; METADATE CD n=155); Study 2, a placebo-controlled, crossover clinical study consisting of 25 pediatric patients (ages 7 to 12 years); and Study 3, an uncontrolled clinical study consisting of 8 pediatric patients (ages 6 to 10 years).

Adverse Reactions Leading to Discontinuation of Treatment

In the 3-week placebo-controlled, parallel-group trial, two METADATE CD-treated patients (1%) and no placebo-treated patients discontinued due to an adverse reaction (rash and pruritus; and headache, abdominal pain, and dizziness, respectively).

Most Common Adverse Reactions

The most common adverse reactions that occurred in 5% or more of patients treated with METADATE CD in a pool of Studies 1, 2 and 3 (ages 6 to 15 years) where the incidence in patients treated with METADATE CD was at least twice the incidence in placebo-treated patients were anorexia and insomnia.

Adverse reactions that occurred in ≥5% of patients treated with METADATE CD and greater than placebo in pooled Studies, 1, 2, and 3 are presented in Table 2:

Table 2: Adverse Reactions (≥5% and Greater than Placebo) in Pediatric Patients Ages 6 to 15 Years Receiving METADATE CD in Pooled Three to Four Week Trials
Body System | Preferred Term | METADATE CD (n=188); % | Placebo (n=190); %
General | Headache | 12 | 8
General | Abdominal Pain (stomachache) | 7 | 4
Digestive System | Anorexia | 9 | 2
Nervous System | Insomnia | 5 | 2

6.2 Postmarketing Experience

The following adverse reactions have been identified during postmarketing use of METADATE CD and other methylphenidate HCl products. Because these reactions are reported voluntarily from a population of uncertain size, it is not possible to reliably estimate their frequency or establish a causal relationship to drug exposure.

Adverse Reactions with METADATE CD

Blood and the lymphatic system disorders:thrombocytopenia

Cardiac disorders:cardiac arrest, sudden death

Immune system disorders:angioedema

Musculoskeletal and connective tissue disorders:rhabdomyolysis

Psychiatric disorders:abnormal behavior, aggression, anxiety, irritability, obsessive-compulsive disorder, suicidal behavior (including completed suicide), libido changes, serotonin syndrome in combination with serotonergic drugs

Nervous System Disorder: migraine, reversible ischemic neurological deficit, bruxism

Skin and subcutaneous tissue disorders:fixed drug eruption

Vascular disorders:peripheral coldness, Raynaud’s phenomenon

Adverse Reactions with Other Methylphenidate HCl Products

Blood and the lymphatic system disorders:leukopenia, anemia, pancytopenia

Cardiac disorders:palpitations; increased blood pressure, tachycardia, angina pectoris, cardiac arrhythmia, myocardial infarction, bradycardia, extrasystole

Eye disorders:blurred vision, difficulties in visual accommodation, diplopia, increased intraocular pressure, mydriasis

Gastrointestinal disorders:nausea, abdominal pain, dry mouth, vomiting, dyspepsia, diarrhea, constipation

General Disorders:fatigue, hyperpyrexia

Hepatobiliary disorders:abnormal liver function, ranging from transaminase elevation to severe hepatic injury

Immune system disorders: hypersensitivity, including anaphylaxis, auricular swelling, bullous conditions, eruptions, exanthemas

Infections and infestations:nasopharyngitis

Metabolism and nutrition disorders:decreased appetite, reduced weight gain and suppression of growth during prolonged use in pediatric patients

Musculoskeletal and connective tissue disorders:arthralgia, muscle cramps, myalgia, muscle twitching

Nervous System Disorder: nervousness, dizziness, headache, dyskinesia, including choreoatheetoid movements, drowsiness, tremor, convulsions, cerebrovascular disorders (including vasculitis, cerebral hemorrhages and cerebrovascular accidents), serotonin syndrome in combination with serotonergic drugs, motor and verbal tics

Psychiatric disorders:depressed mood, restlessness, agitation, psychosis (sometimes with visual and tactile hallucinations), affect liability, mania, disorientation

Renal and urinary disorders:hematuria

Reproductive system and breast disorders:gynecomastia

Respiratory, thoracic and mediastinal disorders:pharyngolaryngeal pain, dyspnea, cough

Skin and subcutaneous tissue disorders:scalp hair loss, hyperhidrosis, angioneurotic edema, erythema, exfoliative dermatitis, thrombocytopenic purpura, urticaria, erythema multiforme rash

Urogenital disorders:priapism

Vascular disorders:isolated cases of cerebral arteritis and/or occlusion

7 DRUG INTERACTIONS

Table 3 presents clinically important drug interactions with METADATE CD.

Table 3: Clinically Important Drug Interactions with METADATE CD
Monoamine Oxidase Inhibitors (MAOI)
Clinical Impact: | Concomitant use of MAOIs and CNS stimulants, including METADATE CD, can cause hypertensive crisis. Potential outcomes include death, stroke, myocardial infarction, aortic dissection, ophthalmological complications, eclampsia, pulmonary edema, and renal failure [see Contraindications (4)] .
Intervention: | Concomitant use of METADATE CD with monoamine oxidase inhibitors (MAOIs) or within 14 days after discontinuing MAOI treatment is contraindicated.
Antihypertensive Drugs
Clinical Impact: | METADATE CD may decrease the effectiveness of drugs used to treat hypertension [see Warnings and Precautions (5.3)] .
Intervention: | Adjust the dosage of the antihypertensive drug as needed.
Halogenated Anesthetics
Clinical Impact: | Concomitant use of halogenated anesthetics and METADATE CD may increase the risk of sudden blood pressure and heart rate increase during surgery.
Intervention: | Monitor blood pressure and avoid use of METADATE CD in patients being treated with anesthetics on the day of surgery.
Risperidone
Clinical Impact: | Combined use of methylphenidate with risperidone when there is a change, whether an increase or decrease, in dosage of either or both medications, may increase the risk of extrapyramidal symptoms (EPS).
Intervention: | Monitor for signs of EPS.

8 USE IN SPECIFIC POPULATIONS

8.1 Pregnancy

There is a pregnancy exposure registry that monitors pregnancy outcomes in women exposed to ADHD medications, including METADATE CD, during pregnancy. Healthcare providers are encouraged to register patients by calling the National Pregnancy Registry for Psychostimulants at 1-866-961-2388.

Risk Summary

Published studies and postmarketing reports on methylphenidate use during pregnancy have not identified a drug-associated risk of major birth defects, miscarriage or adverse maternal or fetal outcomes. There may be risks to the fetus associated with the use of CNS stimulants use during pregnancy (see Clinical Considerations).

No effects on morphological development were observed in embryo-fetal development studies with oral administration of methylphenidate to pregnant rats and rabbits during organogenesis at doses up to 10 and 15 times, respectively, the maximum recommended human dose (MRHD) of 60 mg/day given to adolescents on a mg/m basis. However, spina bifida was observed in rabbits at a dose 53 times the MRHD given to adolescents. A decrease in pup body weight was observed in a pre-and post-natal development study with oral administration of methylphenidate to rats throughout pregnancy and lactation at doses 6 times the MRHD given to adolescents (see Data).

The estimated background risk of major birth defects and miscarriage for the indicated population is unknown. All pregnancies have a background risk of birth defect, loss, or other adverse outcomes. In the U.S. general population, the estimated background risk of major birth defects and miscarriage in clinically recognized pregnancies is 2% to 4% and 15% to 20%, respectively.

Clinical Considerations

Fetal/Neonatal Adverse Reactions

CNS stimulants, such as METADATE CD, can cause vasoconstriction and thereby decrease placental perfusion. No fetal and/or neonatal adverse reactions have been reported with the use of therapeutic doses of methylphenidate during pregnancy; however, premature delivery and low birth weight infants have been reported in amphetamine-dependent mothers.

Animal Data

In embryo-fetal development studies conducted in rats and rabbits, methylphenidate was administered orally at doses of up to 75 and 200 mg/kg/day, respectively, during the period of organogenesis. Malformations (increased incidence of fetal spina bifida) were observed in rabbits at the highest dose, which is approximately 52 times the MRHD of 60 mg/day given to adolescents on a mg/m^2basis. The no effect level for embryo-fetal development in rabbits was 60 mg/kg/day (15 times the MRHD given to adolescents on a mg/m^2basis). There was no evidence of morphological development effects in rats, although increased incidences of fetal skeletal variations were seen at the highest dose level (10 times the MRHD of 60 mg/day given to adults on a mg/m2 basis), which was also maternally toxic. The no effect level for embryo-fetal development in rats was 25 mg/kg/day (3 times the MRHD on a mg/m2 basis). When methylphenidate was administered to rats throughout pregnancy and lactation at doses of up to 45 mg/kg/day, offspring body weight gain was decreased at the highest dose (6 times the MRHD of 60 mg/day given to adults on a mg/m2 basis), but no other effects on postnatal development were observed. The no effect level for pre-and postnatal development in rats was 15 mg/kg/day (~2 times the MRHD given to adolescents on a mg/m2 basis).

8.2 Lactation

Risk Summary

Limited published literature, based on milk sampling from seven mothers reports that methylphenidate is present in human milk, which resulted in infant doses of 0.16% to 0.7% of the maternal weight-adjusted dosage and a milk/plasma ratio ranging between 1.1 and 2.7. There are no reports of adverse effects on the breastfed infant and no effects on milk production. Long-term neurodevelopmental effects on infants from stimulant exposure are unknown. The developmental and health benefits of breastfeeding should be considered along with the mother’s clinical need for METADATE CD and any potential adverse effects on the breastfed infant from METADATE CD or from the underlying maternal condition.

Clinical Considerations

Monitor breastfeeding infants for adverse reactions, such as agitation, insomnia, anorexia, and reduced weight gain.

8.4 Pediatric Use

The safety and effectiveness of METADATE CD have not been established in pediatric patients below the age of 6 years.

In studies evaluating extended-release methylphenidate products, patients 4 to <6 years of age had higher systemic methylphenidate exposures than those observed in older pediatric patients at the same dosage. Pediatric patients 4 to <6 years of age also had a higher incidence of adverse reactions, including weight loss.

The safety and effectiveness of METADATE CD for the treatment of ADHD have been established in pediatric patients 6 to 15 years of age.

Long-Term Suppression of Growth

Growth should be monitored during treatment with stimulants, including Metadate CD. Pediatric patients who are not growing or gaining weight as expected may need to have their treatment interrupted [see Warnings and Precautions (5.6)] .

Juvenile Animal Toxicity Data.

In a study conducted in young rats, methylphenidate was administered orally at doses of up to 100 mg/kg/day for 9 weeks, starting early in the postnatal period (postnatal Day 7) and continuing through sexual maturity (postnatal Week 10). When these animals were tested as adults (postnatal Weeks 13 to 14), decreased spontaneous locomotor activity was observed in males and females previously treated with 50 mg/kg/day (approximately 6 times the MRHD on a mg/m2 basis) or greater, and a deficit in the acquisition of a specific learning task was seen in females exposed to the highest dose (12 times the MRHD on a mg/m2 basis). The no effect level for juvenile neurobehavioral development in rats was 5 mg/kg/day (half the MRHD on a mg/m2 basis). The clinical significance of the long-term behavioral effects observed in rats is unknown.

8.5 Geriatric Use

METADATE CD has not been studied in patients over the age of 65 years.

9 DRUG ABUSE AND DEPENDENCE

9.1 Controlled Substance

METADATE CD contains methylphenidate hydrochloride, a Schedule II controlled substance.

9.2 Abuse

METADATE CD has a high potential for abuse and misuse which can lead to the development of a substance use disorder, including addiction [see Warnings and Precautions (5.1)] . METADATE CD can be diverted for non-medical use into illicit channels or distribution.

Abuse is the intentional non-therapeutic use of a drug, even once, to achieve a desired psychological or physiological effect. Misuse is the intentional use, for therapeutic purposes, of a drug by an individual in a way other than prescribed by a health care provider or for whom it was not prescribed. Drug addiction is a cluster of behavioral, cognitive, and physiological phenomena that may include a strong desire to take the drug, difficulties in controlling drug use (e.g., continuing drug use despite harmful consequences, giving a higher priority to drug use than other activities and obligations), and possible tolerance or physical dependence.

Misuse and abuse of methylphenidate may cause increased heart rate, respiratory rate, or blood pressure; sweating; dilated pupils; hyperactivity; restlessness; insomnia; decreased appetite; loss of coordination; tremors; flushed skin; vomiting; and/or abdominal pain. Anxiety, psychosis, hostility, aggression, and suicidal or homicidal ideation have also been observed with CNS stimulants abuse and/or misuse. Misuse and abuse of CNS stimulants, including METADATE CD, can result in overdose and death [see Overdosage (10)] , and this risk is increased with higher doses or unapproved methods of administration, such as snorting or injection.

9.3 Dependence

Physical Dependence

METADATE CD may produce physical dependence. Physical dependence is a state that develops as a result of physiological adaptation in response to repeated drug use, manifested by withdrawal signs and symptoms after abrupt discontinuation or a significant dose reduction of a drug.

Withdrawal signs and symptoms after abrupt discontinuation or dose reduction following prolonged use of CNS stimulants including METADATE CD include dysphoric mood; depression; fatigue; vivid; unpleasant dreams; insomnia or hypersomnia; increased appetite; and psychomotor retardation or agitation.

Tolerance

METADATE CD may produce tolerance. Tolerance is a physiological state characterized by a reduced response to a drug after repeated administration (i.e., a higher dose of a drug is required to produce the same effect that was once obtained at a lower dose).

10 OVERDOSAGE

Clinical Effects of Overdose

Overdose of CNS stimulants is characterized by the following sympathomimetic effects:

- Cardiovascular effects including tachyarrhythmias, and hypertension or hypotension. Vasospasm, myocardial infarction, or aortic dissection may precipitate sudden cardiac death. Takotsubo cardiomyopathy may develop.
- CNS effects including psychomotor agitation, confusion, and hallucinations. Serotonin syndrome, seizures, cerebral vascular accidents, and coma may occur.
- Life-threatening hyperthermia (temperatures greater than 104ºF) and rhabdomyolysis may develop.

Overdose Management

Consider the possibility of multiple drug ingestion. The pharmacokinetic profile of METADATE CD should be considered when treating patients with overdose. Because methylphenidate has a large volume of distribution and is rapidly metabolized, dialysis is not useful. Consider contacting the Poison Help line (1-800-222-1222) or a medical toxicologist for additional overdose management recommendations.

11 DESCRIPTION

METADATE CD contains methylphenidate hydrochloride, a CNS stimulant. The extended-release capsules comprise both immediate-release (IR) and extended-release (ER) beads such that 30% of the dose is provided by the IR component and 70% of the dose is provided by the ER component. METADATE CD is available in six capsule strengths containing 10 mg (3 mg IR; 7 mg ER), 20 mg (6 mg IR; 14 mg ER), 30 mg (9 mg IR; 21 mg ER), 40 mg (12 mg IR; 28 mg ER), 50 mg (15 mg IR; 35 mg ER), or 60 mg (18 mg IR; 42 mg ER) of methylphenidate hydrochloride for oral administration.

Chemically, methylphenidate HCl is d, l(racemic)- threo-methyl α-phenyl-2-piperidineacetate hydrochloride. Its empirical formula is C14H19NO2•HCl. Its structural formula is:

Methylphenidate HCl USP is a white, odorless, crystalline powder. Its solutions are acid to litmus. It is freely soluble in water and in methanol, soluble in alcohol, and slightly soluble in chloroform and in acetone. Its molecular weight is 269.77.

METADATE CD also contains the following inactive ingredients: Dibutyl sebacate, ethylcellulose aqueous dispersion, gelatin, hydroxypropylmethylcellulose, polyethylene glycol, povidone, sugar spheres, and titanium dioxide.

The individual capsules contain the following color agents:

10 mg capsules: FD&C Blue No. 2, FDA/E172 Yellow Iron Oxide

20 mg capsules: FD&C Blue No. 2

30 mg capsules: FD&C Blue No. 2, FDA/E172 Red Iron Oxide

40 mg capsules: FDA/E172 Yellow Iron Oxide

50 mg capsules: FD&C Blue No. 2, FDA/E172 Red Iron Oxide

12 CLINICAL PHARMACOLOGY

12.1 Mechanism of Action

Methylphenidate hydrochloride is a central nervous system (CNS) stimulant. The mode of therapeutic action in ADHD is not known.

12.2 Pharmacodynamics

Methylphenidate is a racemic mixture comprised of the d-and l-threoenantiomers. The d-threoenantiomer is more pharmacologically active than the l-threoenantiomer. Methylphenidate blocks the reuptake of norepinephrine and dopamine into the presynaptic neuron and increases the release of these monoamines into the extraneuronal space.

12.3 Pharmacokinetics

Following one week of once-daily doses of 20 mg or 40 mg METADATE CD to children aged 7 to12 years old with ADHD, Cmaxand AUC of methylphenidate were approximately proportional to the administered doses.

Absorption

Following administration of METADATE CD in children aged 7 to 12 years old with ADHD, the plasma concentration time profile of methylphenidate showed two phases of drug release with a sharp, initial slope similar to a methylphenidate immediate- release tablet (median T max1 about 1.5 hours post dose), and a second rising portion approximately three hours later (median T max2 about 4.5 hours post dose)*, followed by a gradual decline (Figure 1). The means for Cmaxand area under the curve (AUC) following a dose of 20 mg were slightly lower than those seen with 10 mg of the immediate-release formulation, dosed at 0 and 4 hours.

*25-30% of the subjects had only one observed peak (Cmax) concentration of methylphenidate.

Figure 1: Comparison of Immediate Release (IR) and METADATE CD Formulations After Repeated Doses of Methylphenidate HCl in Pediatric Patients 7 to 12 Years of Age with ADHD

Effect of Food

Ingestion of a high-fat meal with METADATE CD increased the mean Cmaxand AUC of methylphenidate by about 30% and 17%, respectively. The presence of food delayed the early peak by approximately 1 hour (range -2 to 5 hours delay). [ see Dosage and Administration (2.1) ].

The bioavailability (Cmaxand AUC) of methylphenidate was unaffected by sprinkling the METADATE CD capsule contents on applesauce as compared to the intact capsule.

Effect of Alcohol

At an alcohol concentration of 40%, there was an increase in the release rate of methylphenidate in the first hour, resulting in 84% of the methylphenidate being released. The results with the 60 mg capsule are considered to be representative of the other available capsule strengths [see Drug Interactions (7)] .

Distribution

Plasma protein binding is 10% to 33%. The volume of distribution was 2.65 ± 1.11 L/kg for d- methylphenidate and 1.80 ± 0.91 L/kg for l- methylphenidate.

Elimination

The mean terminal half-life (t&frac12;) of methylphenidate following administration of METADATE CD (t&frac12;=6.8 hours) is longer than the mean terminal t&frac12;following administration of methylphenidate hydrochloride immediate-release tablets (t&frac12;=2.9 hours) and methylphenidate hydrochloride extended-release tablets (t&frac12;=3.4 hours) in healthy adult volunteers.

Metabolism

In vitrostudies showed that methylphenidate was not metabolized by cytochrome P450 isoenzymes. Methylphenidate is metabolized primarily by deesterification to alpha-phenyl-piperidine acetic acid (ritalinic acid), which has little or no pharmacologic activity.

Excretion

After oral administration of radiolabeled methylphenidate in humans, about 90% of the radioactivity was recovered in urine. The main urinary metabolite was ritalinic acid, accounting for approximately 80% of the dose.

Specific Populations

Male and Female Patients

The pharmacokinetics of methylphenidate after a single dose of METADATE CD were similar between adult men and women.

Racial or Ethnic Groups

The influence of race on the pharmacokinetics of methylphenidate after METADATE CD administration has not been studied.

Pediatric Patients

The pharmacokinetics of methylphenidate after METADATE CD administration has not been studied in children less than 6 years of age.

Patients with Renal Impairment

METADATE CD has not been studied in patients with renal insufficiency. Since renal clearance is not an important route of methylphenidate clearance, and the major metabolite (ritalinic acid), has little or no pharmacologic activity, renal insufficiency is expected to have minimal effect on the pharmacokinetics of METADATE CD.

Patients with Hepatic Impairment

METADATE CD has not been studied in patients with hepatic insufficiency. Hepatic impairment is expected to have minimal effect on the pharmacokinetics of methylphenidate since it is metabolized primarily to ritalinic acid by nonmicrosomal hydrolytic esterases that are widely distributed throughout the body

Drug Interaction Studies

In vitrostudies showed that methylphenidate did not inhibit cytochrome P450 isoenzymes at clinically observed plasma drug concentrations.

13 NONCLINICAL TOXICOLOGY

13.1 Carcinogenesis, Mutagenesis, Impairment of Fertility

Carcinogenesis

In a lifetime carcinogenicity study carried out in B6C3F1 mice, methylphenidate caused an increase in hepatocellular adenomas and, in males only, an increase in hepatoblastomas, at a daily dose of approximately 60 mg/kg per day. This dose is approximately 2 times the maximum recommended human dose (MRHD) of 60 mg/day given to children on a mg/m^2basis. Hepatoblastoma is a relatively rare rodent malignant tumor type. There was no increase in total malignant hepatic tumors. The mouse strain used is sensitive to the development of hepatic tumors, and the significance of these results to humans is unknown.

Methylphenidate did not cause any increases in tumors in a lifetime carcinogenicity study carried out in F344 rats; the highest dose used was approximately 45 mg/kg/day, which is approximately 4 times the MRHD (children) on a mg/m^2basis.

In a 24-week carcinogenicity study in the transgenic mouse strain p53+/-, which is sensitive to genotoxic carcinogens, there was no evidence of carcinogenicity. Male and female mice were fed diets containing the same concentration of methylphenidate as in the lifetime carcinogenicity study; the high-dose groups were exposed to 60 to 74 mg/kg per day of methylphenidate.

Mutagenesis

Methylphenidate was not mutagenic in the in vitroAmes reverse mutation assay, in the in vitromouse lymphoma cell forward mutation assay, or in the in vitrochromosomal aberration assay using human lymphocytes. Sister chromatid exchanges and chromosome aberrations were increased, indicative of a weak clastogenic response, in an in vitroassay in cultured Chinese Hamster Ovary cells. Methylphenidate was negative in vivoin males and females in the mouse bone marrow micronucleus assay.

Impairment of Fertility

Methylphenidate did not impair fertility in male or female mice that were fed diets containing the drug in an 18-week continuous breeding study. The study was conducted at doses up to 160 mg/kg per day, approximately 10 times the maximum recommended human dose of 60 mg/day given to adolescents on a mg/m^2basis.

14 CLINICAL STUDIES

METADATE CD was evaluated in a double-blind, parallel-group, placebo-controlled trial in which 321 untreated or previously treated pediatric patients with a DSM-IV diagnosis of Attention Deficit Hyperactivity Disorder (ADHD), 6 to 15 years of age, received a single morning dose for up to 3 weeks. Patients were required to have the combined or predominantly hyperactive- impulsive subtype of ADHD; patients with the predominantly inattentive subtype were excluded. Patients randomized to the METADATE CD group received 20 mg daily for the first week. Their dosage could be increased weekly to a maximum of 60 mg by the third week, depending on individual response to treatment.

The patient’s regular school teacher completed the teachers’ version of the Conners’ Global Index Scale (TCGIS), a scale for assessing ADHD symptoms, in the morning and again in the afternoon on three alternate days of each treatment week. The primary efficacy endpoint was determined by the average of the total scores for the 10-item TCGIS completed by the classroom teacher in the morning and again in the afternoon on the three observation days during the last week of double-blind therapy. Patients treated with METADATE CD showed a statistically significant improvement in symptom scores from baseline over patients who received placebo (See Figure 2). Separate analyses of TCGIS scores in the morning and afternoon revealed superiority in improvement with METADATE CD over placebo during both time periods (See Figure 3).

Figure 2: Least Squares Mean Change from Baseline in TCGIS Total Score in Pediatric Patients 6 to 15 years of Age with ADHD

Figure 3: Least Squares Mean Change from Baseline in TCGIS Total Score in Pediatric Patients 6 to 15 years of Age with ADHD: Morning (AM) and Afternoon (PM)

16 HOW SUPPLIED

How Supplied

METADATE CD (methylphenidate HCl, USP) extended-release capsules are available in six strengths (see Table 4):

Table 4: Strengths, Identifying Characteristics, and Packaging Configurations of METADATE CD
Strength | Capsule Color (cap/body) | Imprinting on Capsule Cap | Imprinting on Capsule Body | Capsules per Bottle | NDC Number
10 mg | green/white | “AYTU 579” in white letters | “10 mg” in black letters | 30 | NDC 69654-579-30
20 mg | blue/white | “AYTU 580” in white letters | “20 mg” in black letters | 30 | NDC 69654-580-30
30 mg | reddish- brown/white | “AYTU 581” in white letters | “30 mg” in black letters | 30 | NDC 69654-581-30
40 mg | yellow ivory/white | “AYTU 582” in black letters | “40 mg” in black letters | 30 | NDC 69654-582-30
50 mg | purple/white | “AYTU 583” in white letters | “50 mg” in black letters | 30 | NDC 69654-583-30
60 mg | white/white capsules | “AYTU 584” in black letters | “60 mg” in black letters | 30 | NDC 69654-584-30

Storage and Handling

Store at 25°C (77°F); excursions permitted to 15° to 30°C (59° to 86°F) [See USP Controlled Room Temperature].

17 PATIENT COUNSELING INFORMATION

Advise the patient to read the FDA-approved patient labeling (Medication Guide).

Abuse, Misuse, and Addiction

Educate patients and their families about the risks of abuse, misuse, and addiction of METADATE CD, which can lead to overdose and death, and proper disposal of any unused drug [see Warnings and Precautions (5.1)], Drug Abuse and Dependence (9.2), Overdosage (10)]. Advise patients to store METADATE CD in a safe place, preferably locked, and instruct patients to not give METADATE CD to anyone else.

Administration Instructions

Instruct patients and their caregivers that the METADATE CD capsules and the capsule contents must not be crushed or chewed. Instruct patients that the capsule may be swallowed whole, or alternatively, the capsule may be opened and the capsule contents sprinkled onto a small amount (tablespoon) of applesauce and given immediately, and not stored for future use [see Dosage and Administration (2.3)] .

Risks to Patients with Serious Cardiac Disease

Advise patients that there are potential risks to patients with serious cardiac disease, including sudden death, with METADATE CD use. Instruct patients to contact a healthcare provider immediately if they develop symptoms such as exertional chest pain, unexplained syncope, or other symptoms suggestive of cardiac disease [see Warnings and Precautions (5.2)].

Increased Blood Pressure and Heart Rate

Instruct patients and their caregivers that METADATE CD can cause elevations of their blood pressure and pulse rate [see Warnings and Precautions (5.3)].

Psychiatric Adverse Reactions

Advise patients and their caregivers that METADATE CD, at recommended doses, can cause psychotic or manic symptoms, even in patients without a prior history of psychotic symptoms or mania [see Warnings and Precautions (5.4)].

Priapism

Advise patients and their caregivers of the possibility of painful or prolonged penile erections (priapism). Instruct the patient to seek immediate medical attention in the event of priapism [see Warnings and Precautions (5.5)] .

Circulation Problems in Fingers and Toes (peripheral vasculopathy, including Raynaud’s phenomenon)

- Instruct patients about the risk of peripheral vasculopathy, including Raynaud’s phenomenon, and associated signs and symptoms: fingers or toes may feel numb, cool, painful, and/or may change color from pale, to blue, to red.
- Instruct patients to report to their physician any new numbness, pain, skin color change, or sensitivity to temperature in fingers or toes.
- Instruct patients to call their physician immediately with any signs of unexplained wounds appearing on fingers or toes. Further clinical evaluation (e.g., rheumatology referral) may be appropriate for certain patients [see Warnings and Precautions (5.6)] .

Long-Term Suppression of Growth in Pediatric Patients

Advise patients and their caregivers that METADATE CD can cause slowing of growth and weight loss [see Warnings and Precautions (5.7)].

Increased Intraocular Pressure (IOP) and Glaucoma

Advise patients what IOP and glaucoma may occur during treatment with METADATE CD [see Warnings and Precautions (5.9)] .

Motor and Verbal Tics, and Worsening of Tourette's Syndrome

Advise patients that motor and verbal tics and worsening of Tourette’s Syndrome may occur during treatment with METADATE CD. Instruct patients to notify their healthcare provider if emergence of new tics or worsening of tics or Tourette’s syndrome occurs [see Warnings and Precautions (5.10)] .

Pregnancy Registry

Inform patients that there is a pregnancy exposure registry that monitors pregnancy outcomes in women exposed to METADATE CD during pregnancy [see Use in Specific Populations (8.1) ].

Alcohol Use

Advise patients to avoid alcohol while taking METADATE CD. Consumption of alcohol while taking METADATE CD may result in a more rapid release of the dose of methylphenidate [see Drug Interactions (7)].

Distributed by:
Aytu BioPharma
Denver, CO 80237

METADATE CD is a registered trademark of the Lannett Company, Inc.

MEDICATION GUIDE
METADATE CD®(meh · tuh· dayt CD®)
(methylphenidate)
extended-release capsules, CII

What is the most important information I should know about METADATE CD?
METADATE CD may cause serious side effects, including:

- Abuse, misuse, and addiction.METADATE CD has a high chance for abuse and misuse and may lead to substance use problems, including addiction. Misuse and abuse of METADATE CD, other methylphenidate containing medicines, and amphetamine containing medicines, can lead to overdose and death. The risk of overdose and death is increased with higher doses of METADATE CD or when it is used in ways that are not approved, such as snorting or injection.

- Your healthcare provider should check your child’s risk for abuse, misuse, and addiction before starting treatment with METADATE CD and will monitor your child during treatment.
- METADATE CD may lead to physical dependence after prolonged use, even if taken as directed by your healthcare provider.
- Do not give METADATE CD to anyone else. See “ What is METADATE CD?” for more information.

Keep METADATE CD in a safe place and properly dispose of any unused medicine. See “ How should I store METADATE CD?” for more information.

Tell your healthcare provider if your child has ever abused or been dependent on alcohol, prescription medicines, or street drugs.

- Risks for people with serious heart disease.Sudden death has happened in people who have heart defects or other serious heart disease.

Your healthcare provider should check your child carefully for heart problems before starting treatment with METADATE CD. Tell your healthcare provider if your child has any heart problems, heart disease, or heart defects.

Call your healthcare provider or go to the nearest hospital emergency room right away if your child has any signs of heart problems such as chest pain, shortness of breath, or fainting during treatment with METADATE CD.

- Increased blood pressure and heart rate.

Your healthcare provider should check your child’s blood pressure and heart rate regularly during treatment with METADATE CD.

- Mental (psychiatric) problems, including:

- new or worse behavior and thought problems
- new or worse bipolar illness
- new psychotic symptoms (such as hearing voices, or seeing or believing things that are not real) or new manic symptoms

Tell your healthcare provider about any mental problems your child has, or about a family history of, suicide, bipolar illness, or depression.

Call your healthcare provider right away if your child has any new or worsening mental symptoms or problems during treatment with METADATE CD, especially hearing voices, seeing or believing things that are not real, or new manic symptoms.

What is METADATE CD?

METADATE CD is a prescription medicine used for the treatment of Attention Deficit Hyperactivity Disorder (ADHD) in children 6 to 15 years of age. METADATE CD may help increase attention and decrease impulsiveness and hyperactivity in people with ADHD.

METADATE CD is not recommended for use in children under 6 years of age with ADHD.

METADATE CD is a federally controlled substance (CII) because it contains methylphenidate that can be a target for people who abuse prescription medicines or street drugs.

Keep METADATE CD in a safe place to protect it from theft. Never give your METADATE CD to anyone else, because it may cause death or harm them. Selling or giving away METADATE CD may harm others and is against the law.

Who should not take METADATE CD?

Your child should not take METADATE CD if your child:

- is allergic to methylphenidate hydrochloride or any of the ingredients in METADATE CD. See the end of this Medication Guide for a complete list of ingredients in METADATE CD.
- has a rare inherited problem with the breaking down, absorbing, and processing of certain types of sugar in the body. METADATE CD contains a type of sugar called sucrose.
- is taking, or has stopped taking within the past 14 days, a medicine called a monoamine oxidase inhibitor (MAOI).

Before starting METADATE CD tell your healthcare provider about all your child’s medical conditions, including: if your child:

- has heart problems, heart disease, heart defects, or high blood pressure
- has mental problems including psychosis, mania, bipolar illness, or depression or has a family history of suicide, bipolar illness, or depression
- has circulation problems in fingers and toes
- have eye problems, including increased pressure in your eye, glaucoma, or problems with your close-up vision (farsightedness)
- have or had repeated movements or sounds (tics) or Tourette’s syndrome, or have a family history of tics or Tourette’s syndrome
- is pregnant or plan to become pregnant. It is not known if METADATE CD will harm the unborn baby.
  - There is a pregnancy registry for females who are exposed to METADATE CD during pregnancy. The purpose of the registry is to collect information about the health of females exposed to METADATE CD and their baby. If you or your child becomes pregnant during treatment with METADATE CD, talk to your healthcare provider about registering with the National Pregnancy Registry for Psychostimulants at 1-866-961-2388.
- is breastfeeding or plan to breastfeed. METADATE CD passes into breast milk. Talk to your healthcare provider about the best way to feed the baby during treatment with METADATE CD.

Tell your healthcare provider about all the medicines that your child takes,including prescription and over-the- counter medicines, vitamins, and herbal supplements.

METADATE CD and some medicines may interact with each other and cause serious side effects. Sometimes the doses of other medicines will need to be changed during treatment with METADATE CD. Your healthcare provider will decide whether METADATE CD can be taken with other medicines.

Especially tell your healthcare provider if your child takesa medicine used to treat depression called a monoamine oxidase inhibitor (MAOI).

Know the medicines that your child takes. Keep a list of the medicines with you to show your healthcare provider and pharmacist. Your child should not start taking any new medicines during treatment with METADATE CD without talking to your healthcare provider first.

How should METADATE CD be taken?

- Take METADATE CD exactly as prescribed by your healthcare provider.
- Your healthcare provider may change the dose if needed.
- Take METADATE CD 1 time each day in the morning before breakfast.
- Swallow METADATE CD capsules whole with water or other liquids.
- If METADATE CD capsules cannot be swallowed whole, the capsule may be opened and the contents sprinkled onto a tablespoonful of applesauce.
  - Follow with a drink of water or other liquid.
  - Do notchew the applesauce and medicine mixture.
  - Swallow all the applesauce and medicine mixture right away. Do notstore the applesauce and medicine mixture.

If your child takes too much METADATE CD, call your healthcare provider or Poison Help line at 1-800-222-1222 or go to the nearest hospital emergency room right away.

What should be avoided during treatment with METADATE CD?

Avoid drinking alcohol during treatment with METADATE CD. This may cause a faster release of the METADATE CD medicine.

What are the possible side effects of METADATE CD?

METADATE CD may cause serious side effects, including:

- See “ What is the most important information I should know about METADATE CD?”
- Painful and prolonged erections (priapism).Priapism has happened in males who take products that contain methylphenidate. If your child develops priapism, get medical help right away.
- Circulation problems in fingers and toes (peripheral vasculopathy, including Raynaud’s phenomenon).Signs and symptoms may include:
  - fingers or toes may feel numb, cool, painful
  - fingers or toes may change color from pale, to blue, to red
  Tell your healthcare provider if your child has numbness, pain, skin color change, or sensitivity to temperature in the fingers or toes.
  Call your healthcare provider right awayif your child has any signs of unexplained wounds appearing on the fingers or toes during treatment with METADATE CD.
- Slowing of growth (height and weight) in children.Children should have their height and weight checked often during treatment with METADATE CD. METADATE CD treatment may be stopped if your child is not growing or gaining weight.
- Eye problems (increased pressure in the eye and glaucoma).Call your healthcare provider right away if you or your child develop changes in your vision or eye pain, swelling, or redness.
- New or worsening tics or worsening Tourette’s syndrome.Tell your healthcare provider if you or your child get any new or worsening tics or worsening Tourette’s syndrome during treatment with METADATE CD.

The most common side effects of METADATE CD includeanorexia and trouble sleeping. These are not all the possible side effects of METADATE CD.

Call your doctor for medical advice about side effects. You may report side effects to FDA at 1-800-FDA-1088.

How should I store METADATE CD?

- Store METADATE CD at room temperature between 68°F to 77°F (20°C to 25°C).
- Store METADATE CD in a safe place, like a locked cabinet. Protect from light and moisture.
- Dispose of remaining, unused, or expired METADATE CD by a medicine take-back program at a U.S. Drug Enforcement Administration (DEA) authorized collection site. If no take-back program or DEA authorized collector is available, mix METADATE CD with an undesirable, nontoxic substance such as dirt, cat litter, or used coffee grounds to make it less appealing to children and pets. Place the mixture in a container such as a sealed plastic bag and throw away METADATE CD in the household trash. Visit www.fda.gov/drugdisposal for additional information on disposal of unused medicines.

Keep METADATE CD and all medicines out of the reach of children

General information about the safe and effective use of METADATE CD.

Medicines are sometimes prescribed for purposes other than those listed in a Medication Guide. Do not use METADATE CD for a condition for which it was not prescribed. Do not give METADATE CD to other people, even if they have the same symptoms. It may harm them and it is against the law. You can ask your healthcare provider or pharmacist for information about METADATE CD that is written for healthcare professionals.

What are the ingredients in METADATE CD?

Active Ingredient:methylphenidate hydrochloride

Inactive Ingredients:sugar spheres, povidone, hydroxypropylmethylcellulose and polyethylene glycol, ethylcellulose aqueous dispersion, dibutyl sebacate, gelatin, and titanium dioxide.

The individual capsules contain the following coloring agents:

10 mg capsules: FD&C Blue No. 2, FDA/E172 Yellow Iron Oxide

20 mg capsules: FD&C Blue No. 2

30 mg capsules: FD&C Blue No. 2, FDA/E172 Red Iron Oxide 40 mg capsules: FDA/E172 Yellow Iron Oxide

50 mg capsules: FD&C Blue No. 2, FDA/E172 Red Iron Oxide

Distributed by:
Aytu BioPharma
Denver, CO 80237

METADATE CD is a registered trademark of the Lannett Company, Inc.

For more information about METADATE CD call 1-855-298-8246.

This Medication Guide has been approved by the U.S. Food and Drug Administration

Revised 9/2025

PRINCIPAL DISPLAY PANEL - 10 MG BOTTLE

NDC 69654-579-30

Once Daily

CII

Metadate CD®

10 mg

A Medication Guide is required
for every prescription dispensed.
Please use accompanying Medication Guide.

Rx Only
100 Capsules

PRINCIPAL DISPLAY PANEL - 20 MG BOTTLE

NDC 69654-580-30

Once Daily

CII

Metadate CD®

20 mg

A Medication Guide is required
for every prescription dispensed.
Please use accompanying Medication Guide.

Rx Only
100 Capsules

PRINCIPAL DISPLAY PANEL - 30 MG BOTTLE

NDC 69654-581-30

Once Daily

CII

Metadate CD®

30 mg

A Medication Guide is required
for every prescription dispensed.
Please use accompanying Medication Guide.

Rx Only
100 Capsules

PRINCIPAL DISPLAY PANEL - 40 MG BOTTLE

NDC 69654-582-30

Once Daily

CII

Metadate CD®

40 mg

A Medication Guide is required
for every prescription dispensed.
Please use accompanying Medication Guide.

Rx Only
100 Capsules

PRINCIPAL DISPLAY PANEL - 50 MG BOTTLE

NDC 69654-583-30

Once Daily

CII

Metadate CD®

50 mg

A Medication Guide is required
for every prescription dispensed.
Please use accompanying Medication Guide.

Rx Only
100 Capsules

PRINCIPAL DISPLAY PANEL - 60 MG BOTTLE

NDC 69654-584-30

Once Daily

CII

Metadate CD®

60 mg

A Medication Guide is required
for every prescription dispensed.
Please use accompanying Medication Guide.

Rx Only
100 Capsules